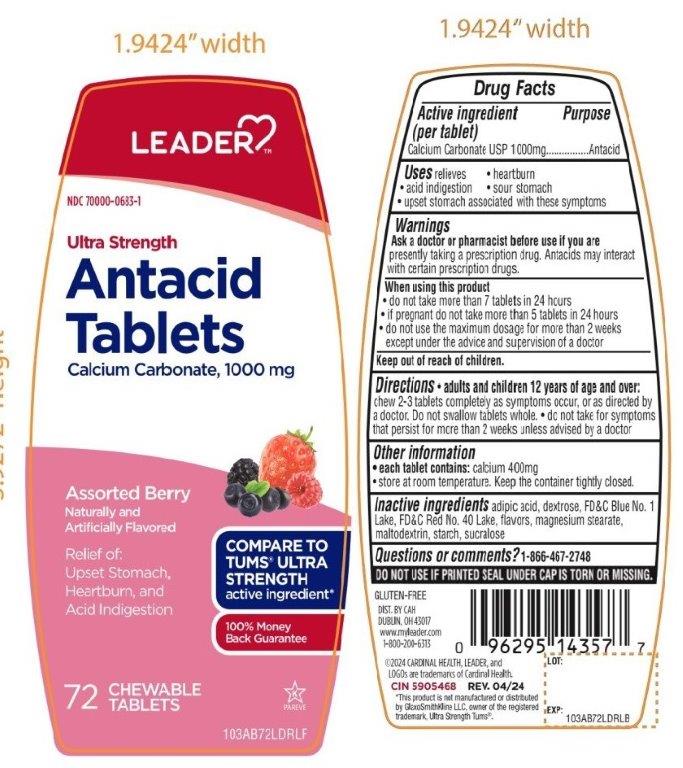 DRUG LABEL: ANTACID

NDC: 70000-0683 | Form: TABLET, CHEWABLE
Manufacturer: CARDINAL HEALTH 110, LLC.
Category: otc | Type: HUMAN OTC DRUG LABEL
Date: 20251014

ACTIVE INGREDIENTS: CALCIUM CARBONATE 1000 mg/1 1
INACTIVE INGREDIENTS: ADIPIC ACID; DEXTROSE, UNSPECIFIED FORM; FD&C BLUE NO. 1; FD&C RED NO. 40; MAGNESIUM STEARATE; MALTODEXTRIN; STARCH, CORN; SUCRALOSE

LEADER Ultra Strength Antacid Tablets Drug Facts

Active ingredient (per tablet)

Calcium Carbonate USP 1000mg

Purpose

Antacid

Uses

relieves

- heartburn
- acid indigestion
- sour stomach
- upset stomach associated with these symptoms

Ask a doctor or pharmacist before use if you are

presently taking a prescription drug. Antacids may interact with certain prescription drugs.

When using this product

- do not take more than 7 tablets in 24 hours
- if pregnant do not take more than 5 tablets in 24 hours
- do not use the maximum dosage for more than 2 weeks except under the advice and supervision of a doctor

Directions

- adults and children 12 years of age and over:chew 2-3 tablets completely as symptoms occur, or as directed by a doctor. Do not swallow tablets whole.
- do not take for symptoms that persist for more than 2 weeks unless advised by a doctor

Other information

- each tablet contains:calcium 400mg
- store at room temperature. Keep the container tightly closed.

Inactive ingredients

adipic acid, dextrose, FD&C Blue No. 1, FD&C Red No. 40, flavors, magnesium stearate, maltodextrin, starch, sucralose.

Questions or comments?

1-866-467-2748

DO NOT USE IF PRINTED SEAL UNDER CAP IS TORN OR MISSING

Package/Label Principal Display Panel

LEADER™

NDC 70000-683-1

COMPARE TO TUMS®ULTRA STRENGTH active ingredient*

Ultra Strength

Antacid Tablets

Calcium Carbonate 1000 mg

Assorted Berry

Naturally and Artificially Flavored

Relief of:

- Acid Indigestion
- Upset Stomach
- Heartburn

GLUTEN FREE

72 CHEWABLE TABLETS

K PAREVE

100% Money Back Guarantee

DIST. BY: CAH

DUBLIN, OH 43017

www.myleader.com

1-800-200-6313

©2024 CARDINAL HEALTH, LEADER and

LOGOs are trademarks of Cardinal Health.

CIN 5905468

REV. 04/24

*This product is not manufactured or distributed by GlaxoSmithKline LLC, owner of the registered trademark, Ultra Strength Tums®.